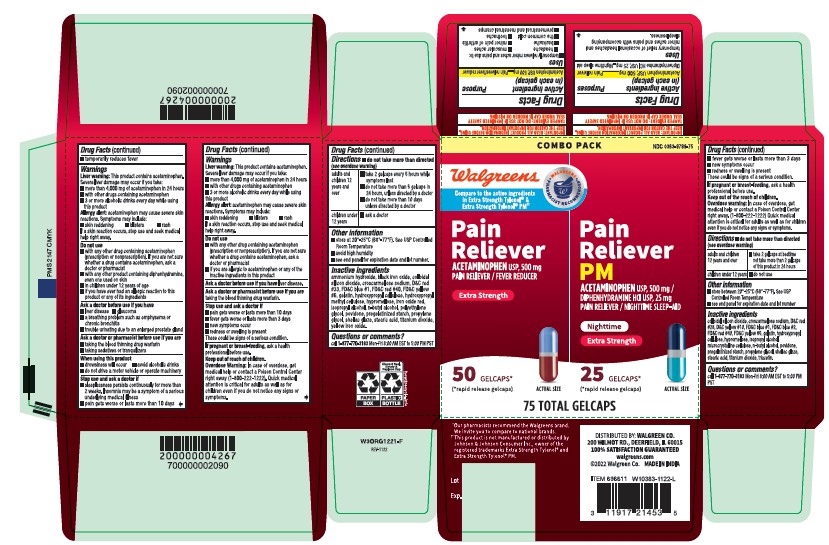 DRUG LABEL: Acetaminophen Diphenhydramine HCL
NDC: 0363-9799 | Form: TABLET
Manufacturer: WALGREEN CO.
Category: otc | Type: HUMAN OTC DRUG LABEL
Date: 20251219

ACTIVE INGREDIENTS: ACETAMINOPHEN 500 mg/1 1; DIPHENHYDRAMINE HYDROCHLORIDE 25 mg/1 1
INACTIVE INGREDIENTS: TRIACETIN; HYDROXYPROPYL CELLULOSE, UNSPECIFIED; FD&C BLUE NO. 2; D&C RED NO. 28; GELATIN; BUTYL ALCOHOL; SHELLAC; STEARIC ACID; MICROCRYSTALLINE CELLULOSE; AMMONIA; FD&C RED NO. 40; POLYETHYLENE GLYCOL, UNSPECIFIED; FERRIC OXIDE RED; STARCH, CORN; PROPYLENE GLYCOL; D&C YELLOW NO. 10; CROSCARMELLOSE SODIUM; D&C RED NO. 33; FD&C BLUE NO. 1; TITANIUM DIOXIDE; FERROSOFERRIC OXIDE; SILICON DIOXIDE; FD&C YELLOW NO. 6; HYPROMELLOSE, UNSPECIFIED; ISOPROPYL ALCOHOL; POVIDONE; FERRIC OXIDE YELLOW

Combo Pack
Pain reliever Acetaminophen USP, 500mg
Pain releiver/fever reducer
Extra strength
Pain reliever PM
Acetaminophen USP, 500mg/Diphenhydramine HCL USP, 25mg
Pain reliever/ Nighttime sleep-aid
Nighttime
Extra strength

Acetaminophen Gelcaps Active Ingredient (in each Gelcap)

Acetaminophen USP, 500 mg

Purpose

Pain reliever/fever reducer

Uses

■ temporarily relieves minor aches and pains due to:

■ headache

■ muscular aches

■ backache

■ minor pain of arthritis

■ the common cold

■ toothache

■ premenstrual and menstrual cramps

■ temporarily reduces fever

Liver Warning

This product contains acetaminophen. Severe liver damage may occur if you take:

■ more than 4,000 mg of acetaminophen in 24 hours

■ with other drugs containing acetaminophen

■ 3 or more alcoholic drinks every day while using this product

Allergy Alert

acetaminophen may cause severe skin reactions. Symptoms may include:

■ skin reddening

■ blisters

■ rash

If a skin reaction occurs, stop use and seek medical help right away.

Do not use

■ with any other drug containing acetaminophen (prescription or nonprescription). If you are not sure whether a drug contains acetaminophen, ask a doctor or pharmacist

■ if you have ever had an allergic reaction to this product or any of its ingredients

Ask a doctor before use if you have

liver disease

Ask a doctor or pharmacist before use if you are

taking the blood thinning drug warfarin.

Stop use and ask doctor if

■ pain gets worse or lasts more than 10 days

■ fever gets worse or lasts more than 3 days

■ new symptoms occur

■ redness or swelling is present

These could be signs of a serious condition.

If pregnant or breast-feeding

ask a health professional before use.

Keep out of the reach of children.

Overdose Warning

In case of accidental overdose, get medical help or contact a Poison Control Center (1-800-222-1222) right away. Prompt medical attention is critical for adults as well as for children even if you do not notice any signs or symptoms.

Directions

■ do not take more than directed (see overdose warning)

adults and children 12 years and over

■ take 2 gelcaps every 6 hours while symptoms last

■ do not take more than 6 gelcaps in 24 hours, unless directed by a doctor

■ do not take more than 10 days unless directed by a doctor

children under 12 years

■ ask a doctor

Other information

■ store at 20°-25°C (68°-77°F). See USP Controlled Room Temperature

■ avoid high humidity

■ see end panel for lot number and expiration date

Inactive ingredients

ammonium hydroxide, black iron oxide, colloidal silicon dioxide, croscarmellose sodium, D&C red#33, FD&C blue#1, FD&C red#40, FD&C yellow#6, gelatin, hydroxypropyl cellulose, hydroxypropyl methyl cellulose, hypromellose, iron oxide red, isopropyl alcohol, n-butyl alcohol, polyethylene glycol, povidone, pregelatinized starch, propylene glycol, shellac glaze, stearic acid, titanium dioxide, yellow iron oxide.

Questions or comments?

call 1-877-770-3183 Mon-Fri 8:00 AM EST to 5:00 PM PST.

Acetaminophen PM Gelcaps Active ingredient (in each gelcap)

Acetaminophen USP, 500 mg

Diphenhydramine HCl USP, 25 mg

Purposes

Pain reliever

Nighttime sleep aid

Uses

temporary relief of occasional headaches and minor aches and pains with accompanying sleeplessness

Liver warning

This product contains acetaminophen. Severe liver damage may occur if you take

■ more than 4,000 mg of acetaminophen in 24 hours

■ with other drugs containing acetaminophen

■ 3 or more alcoholic drinks every day while using this product

Allergy alert

acetaminophen may cause severe skin reactions. Symptoms may include:

■ skin reddening

■ blisters

■ rash

If a skin reaction occurs, stop use and seek medical help right away.

Do not use

■ with any other drug containing acetaminophen (prescription or nonprescription). If you are not sure whether a drug contains acetaminophen, ask a doctor or pharmacist.

■ with any other product containing diphenhydramine, even one used on skin

■ in children under 12 years of age

■ if you have ever had an allergic reaction to this product or any of its ingredients

Ask a doctor before use if you have

■ liver disease

■ a breathing problem such as emphysema or chronic bronchitis

■ trouble urinating due to an enlarged prostate gland

■ glaucoma

Ask a doctor or pharmacist before use if you are

■ taking the blood thinning drug warfarin

■ taking sedatives or tranquilizers

When using this product

■ drowsiness will occur

■ avoid alcoholic drinks

■ do not drive a motor vehicle or operate machinery

Stop use and ask doctor if

■ sleeplessness persists continuously for more than 2 weeks. Insomnia may be a symptom of serious underlying medical illness.

■ pain gets worse or lasts more than 10 days

■ fever gets worse or lasts more than 3 days

■ redness or swelling is present

■ new symptoms occur

These could be signs of a serious condition.

If pregnant or breast-feeding,

ask a health professional before use.

Keep out of the reach of children.

Overdose warning

Taking more than the recommended dose (overdose) may cause liver damage. In case of overdose, get medical help or contact a Poison Control Center (1-800-222-1222) right away. Quick medical attention is critical for adults as well as for children even if you do not notice any signs or symptoms.

Directions

■ do not take more than directed (see overdose warning)

adults and children 12 years and over

■ take 2 gelcaps at bedtime

■ do not take more than 2 gelcaps of this product in 24 hours

children under 12 years

■ do not use

Other information

■ store between 20°-25°C (68°-77°F). See USP Controlled Room Temperature.

■ see end panel for lot number and expiration date

Inactive ingredients

colloidal silicon dioxide, croscarmellose sodium, D7C red#28, D&C yellow#10, FD7C blue#1, FD&C blue #2, FD&C red #40, FD&C yellow #6, gelatin, hydroxypropyl cellulose, hypromellose, isopropyl alcohol, microcrystalline cellulose, n-butyl alcohol, povidone, pregelatinized starch, propylene glycol, shellac glaze, stearic acid, titanium dioxide, triacetin.

Questions or comments?

call 1-877-770-3183 Mon-Fri 8:00 AM EST to 5:00 PM PST.